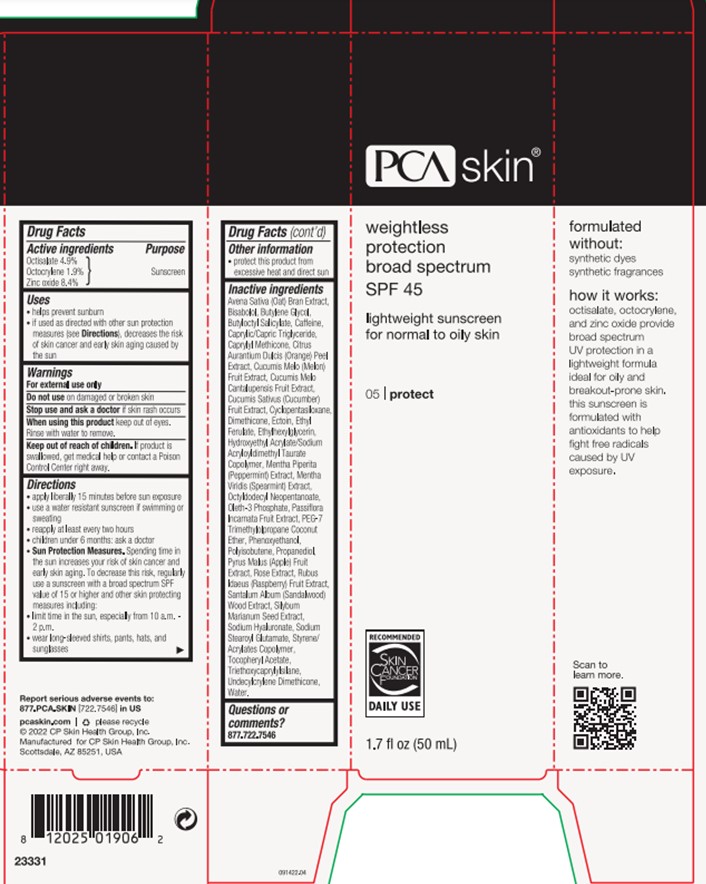 DRUG LABEL: Weightless Protection
NDC: 68726-262 | Form: LOTION
Manufacturer: CP Skin Health Group, Inc.
Category: otc | Type: HUMAN OTC DRUG LABEL
Date: 20240214

ACTIVE INGREDIENTS: OCTOCRYLENE 2 g/100 mL; OCTISALATE 5 g/100 mL; ZINC OXIDE 8.4 g/100 mL
INACTIVE INGREDIENTS: APPLE; HYDROXYETHYL ACRYLATE/SODIUM ACRYLOYLDIMETHYL TAURATE COPOLYMER (100000 MPA.S AT 1.5%); ECTOINE; BUTYLOCTYL SALICYLATE; BUTYLENE GLYCOL; SILYBUM MARIANUM SEED; CANTALOUPE; MUSKMELON; UNDECYLCRYLENE DIMETHICONE (10000 MW); WATER; ORANGE PEEL; ALPHA-TOCOPHEROL ACETATE; HYALURONATE SODIUM; OAT BRAN; LEVOMENOL; PHENOXYETHANOL; ETHYLHEXYLGLYCERIN; OLETH-3 PHOSPHATE; CYCLOMETHICONE 5; ETHYL FERULATE; TRIETHOXYCAPRYLYLSILANE; MEDIUM-CHAIN TRIGLYCERIDES; DIMETHICONE; OCTYLDODECYL NEOPENTANOATE; SODIUM STEAROYL GLUTAMATE; CAPRYLYL TRISILOXANE; MENTHA SPICATA WHOLE; STYRENE/ACRYLAMIDE COPOLYMER (MW 500000); POLYISOBUTYLENE (1000 MW); CUCUMBER; PASSIFLORA INCARNATA FRUIT; PROPANEDIOL; CAFFEINE; MENTHA X PIPERITA WHOLE; SANDALWOOD; RASPBERRY

PCA Skincare Weightless Protections SPF 45

Active Ingredients

Octisalate (4.9%)

Octocrylene (1.9%)

Zinc Oxide (8.4%)

Purpose

Sunscreen

Uses

Helps prevent sunburn

If used as directed with other sun protection measures (see Directions), decreases the risk of skin cancer and early skin aging caused by the sun

Uses

Helps prevent sunburn

If used as directed with other sun protection measures (see Directions), decreases the risk of skin cancer and early skin aging caused by the sun

Warnings

For external use only.

Do not use on damaged or broken skin.

Stop use and ask a doctor if skin rash occurs.

When using this product keep out of eyes. Rinse with water to remove

Keep out of reach of children. If product is swallowed, get medical help or contact a Poison Control Center right away.

Directions

Apply liberally 15 minutes before sun exposure.

Use a water resistant sunscreen if swimming or sweating

Reapply at least every two hours

Children under 6 months: ask a doctor

Sun Protectin Measures. Spending time in the sun increases your risk of skin cancer and early skin aging. To decrease this risk, regularly use a sunscreen with a broad spectrum SPF value of 15 or higher and other skin protecting measures including: limit time in the sun, especially from 10 a.m. - 2 p.m., wear long sleeved shirts, pants, hats and sunglasses.

Other Information

Protect this product from excessive heat and direct sun

Inactive Ingredients

Avena Sativa (Oat) Bran Extract

Bisabolol

Butylene Glycol

Butyloctyl Salicylate

Caffeine

Caprylic/Capric Triglyceride

Caprylyl Methicone

Citrus Aurantium Dulcis (Orange) Peel Extract

Cucumis Melo Cantalupensis Fruit Extract

Cucumis Melo (Melon) Fruit Extract

Cucumis Sativus (Cucumber) Fruit Extract

Cyclopentasiloxane

Dimethicone

Ectoin

Ethyl Ferulate

Ethylhexylglycerin

Hydroxyethyl Acrylate/Sodium Acryloyldimethyl Taurate Copolymer

Mentha Piperita (Peppermint) Extract

Mentha Viridis (Spearmint) Extract

Octyldodecyl Neopentanoate

Oleth-3 Phosphate

Passiflora Incarnata Fruit Extract

PEG-7 Trimethylolpropane Coconut Ether

Phenoxyethanol

Polyisobutene

Propanediol

Pyrus Malus (Apple) Fruit Extract

Rubus Idaeus (Raspberry) Fruit Extract

Rose Extract

Santalum Album (Sandalwood) Wood Extract

Silybum Marianum Seed Extract

Sodium Hyaluronate

Sodium Stearoyl Glutamate

Styrene/Acrylates Copolymer

Tocopheryl Acetate

Triethoxycaprylylsilane

Undecylcrylene Dimethicone

Water

Questions

Please call 877.722.7546